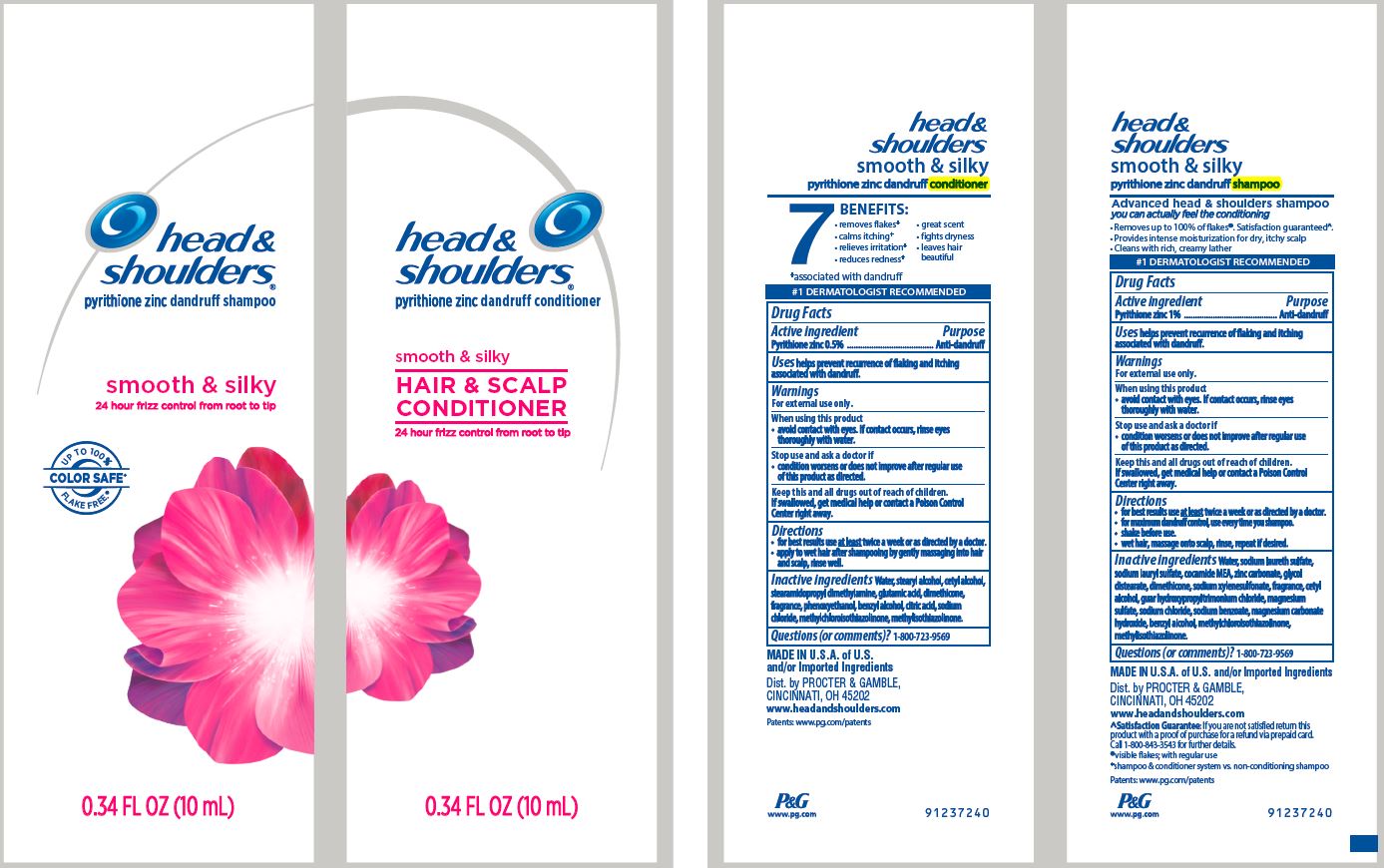 DRUG LABEL: Head and Shoulders Dual Sachets
NDC: 69423-296 | Form: KIT | Route: TOPICAL
Manufacturer: The Procter & Gamble Manufacturing Company
Category: otc | Type: HUMAN OTC DRUG LABEL
Date: 20200109

ACTIVE INGREDIENTS: PYRITHIONE ZINC 1 g/100 mL; PYRITHIONE ZINC 0.5 g/100 mL
INACTIVE INGREDIENTS: GUAR HYDROXYPROPYLTRIMONIUM CHLORIDE (1.7 SUBSTITUENTS PER SACCHARIDE); WATER; SODIUM LAURETH-3 SULFATE; SODIUM LAURYL SULFATE; COCO MONOETHANOLAMIDE; ZINC CARBONATE; GLYCOL DISTEARATE; SODIUM XYLENESULFONATE; DIMETHICONE; CETYL ALCOHOL; MAGNESIUM SULFATE, UNSPECIFIED FORM; SODIUM CHLORIDE; SODIUM BENZOATE; MAGNESIUM CARBONATE HYDROXIDE; BENZYL ALCOHOL; METHYLCHLOROISOTHIAZOLINONE; METHYLISOTHIAZOLINONE; WATER; STEARYL ALCOHOL; CETYL ALCOHOL; STEARAMIDOPROPYL DIMETHYLAMINE; DIMETHICONE; GLUTAMIC ACID; PHENOXYETHANOL; BENZYL ALCOHOL; CITRIC ACID MONOHYDRATE; SODIUM CHLORIDE; METHYLCHLOROISOTHIAZOLINONE; METHYLISOTHIAZOLINONE

Head and Shoulders® Dual Sachets
Smooth and Silky

head &
shoulders
instant relief
pyrithione zinc dandruff shampoo

Drug Facts

Active ingredient

Pyrithione zinc 1%

Purpose

Anti-dandruff

Uses

helps prevent recurrence of flaking and itching associated with dandruff.

Warnings

For external use only.

When using this product

- avoid contact with eyes. If contact occurs, rinse eyes thoroughly with water.

Stop use and ask a doctor if

- condition worsens or does not improve after regular use of this product as directed.

KEEP OUT OF REACH OF CHILDREN

Keep this and all drugs out of reach of children.

If swallowed, get medical help or contact a Poison Control Center right away.

Directions

- for best results use at least twice a week or as directed by a doctor.
- for maximum dandruff control, use every time you shampoo.
- shake before use.
- wet hair, massage onto scalp, rinse, repeat if desired.

Inactive ingredients

Water, sodium laureth sulfate, sodium lauryl sulfate, cocamide MEA, zinc carbonate, glycol distearate, fragrance, sodium xylenesulfonate, dimethicone, cetyl alcohol, guar hydroxypropyltrimonium chloride, magnesium sulfate, sodium chloride, sodium benzoate, magnesium carbonate hydroxide, benzyl alcohol, mentha piperita (peppermint) oil, menthol, mentha arvensis leaf oil, methylchloroisothiazolinone, methylisothiazolinone, yellow 5, blue 1.

Questions (or comments)?

1-800-723-9569

head &
shoulders
instant relief
pyrithione zinc dandruff conditioner

Drug Facts

Active ingredient

Pyrithione zinc 0.5%

Purpose

Anti-dandruff

Uses

helps prevent recurrence of flaking and itching associated with dandruff.

Warnings

For external use only.

When using this product

- avoid contact with eyes. If contact occurs, rinse eyes thoroughly with water.

Stop use and ask a doctor if

- condition worsens or does not improve after regular use of this product as directed.

KEEP OUT OF REACH OF CHILDREN

Keep this and all drugs out of reach of children.

If swallowed, get medical help or contact a Poison Control Center right away.

Directions

- for best results use at least twice a week or as directed by a doctor.
- apply to wet hair after shampooing by gently massaging into hair and scalp, rinse well.

Inactive ingredients

Water, stearyl alcohol, cetyl alcohol, stearamidopropyl dimethylamine, fragrance, dimethicone, glutamic acid, phenoxyethanol, benzyl alcohol, citric acid, sodium chloride, mentha piperita (peppermint) oil, menthol, mentha arvensis leaf oil, methylchloroisothiazolinone, methylisothiazolinone, yellow 5, blue 1.

Questions (or comments)?

1-800-723-9569

Dist. by PROCTER & GAMBLE,
CINCINNATI, OH 45202

PRINCIPAL DISPLAY PANEL - Kit Package

head &
shoulders®

pyrithione zinc dandruff shampoo

smooth & silky

24 hour frizz control from root to tip

FLAKE FREE.*
UP TO 100%
COLOR SAFE

0.34 FL OZ (10 mL)

head &
shoulders®

pyrithione zinc dandruff conditioner

smooth & silky

24 hour frizz control from root to tip

0.34 FL OZ (10 mL)